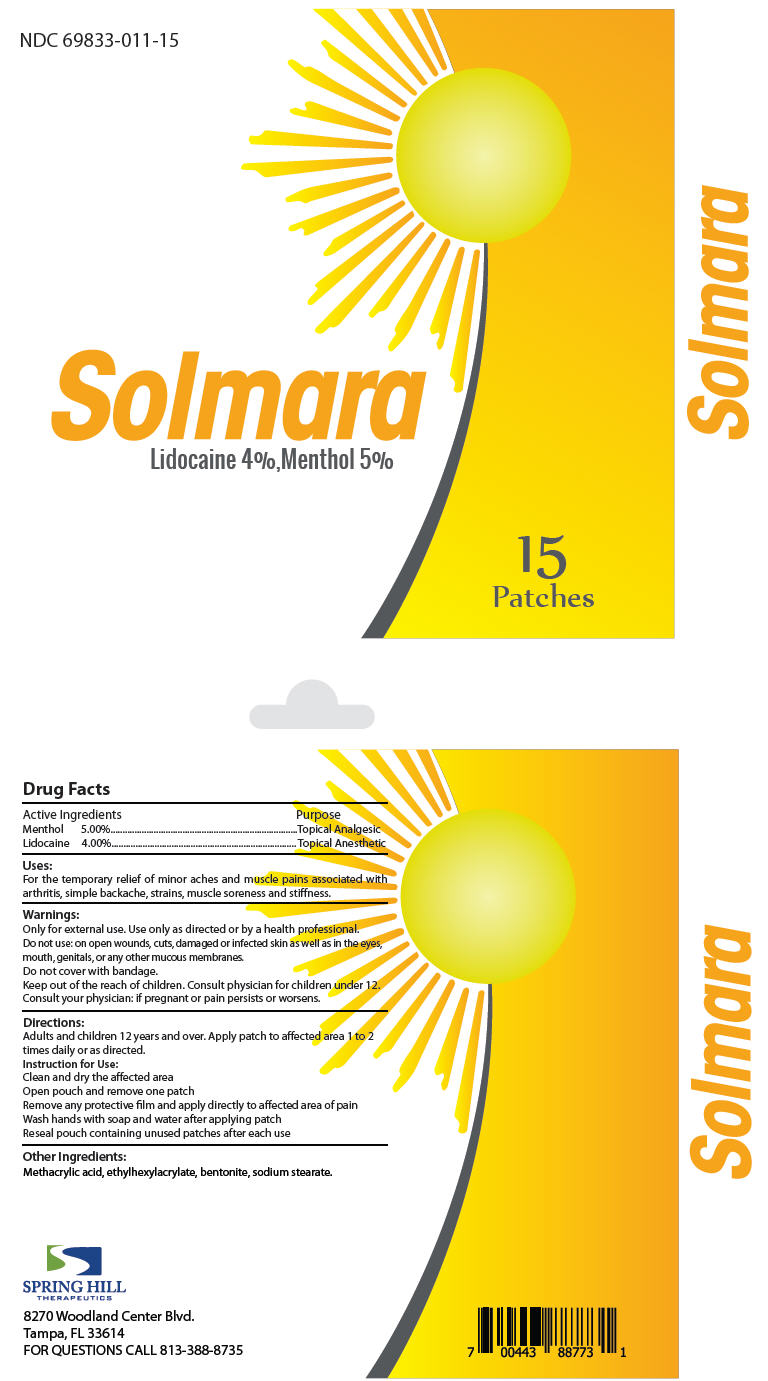 DRUG LABEL: Solmara
NDC: 69833-011 | Form: PATCH
Manufacturer: Spring Hill Therapeutics LLC
Category: otc | Type: HUMAN OTC DRUG LABEL
Date: 20150721

ACTIVE INGREDIENTS: Menthol, Unspecified Form 5 g/1 1; Lidocaine 4 g/1 1
INACTIVE INGREDIENTS: 2-Ethylhexyl Acrylate; Methacrylic Acid; Bentonite; Sodium Stearate

Solmara

Drug Facts

ACTIVE INGREDIENT

Active Ingredients |  | Purpose
Menthol | 5.00% | Topical Analgesic
Lidocaine | 4.00% | Topical Anesthetic

Uses

For the temporary relief of minor aches and muscle pains associated with arthritis, simple backache, strains, muscle soreness and stiffness.

Warnings

WHEN USING

Only for external use. Use only as directed or by a health professional.

Do not use: on open wounds, cuts, damaged or infected skin as well as in the eyes, mouth, genitals, or any other mucous membranes.

Do not cover with bandage.

KEEP OUT OF REACH OF CHILDREN

Keep out of the reach of children. Consult physician for children under 12.

PREGNANCY OR BREAST FEEDING

Consult your physician: if pregnant or pain persists or worsens.

Directions

Adults and children 12 years and over. Apply patch to affected area 1 to 2 times daily or as directed.

Instruction for Use

Clean and dry the affected area

Open pouch and remove one patch

Remove any protective film and apply directly to affected area of pain

Wash hands with soap and water after applying patch

Reseal pouch containing unused patches after each use

Other Ingredients

Methacrylic acid, ethylhexylacrylate, bentonite, sodium stearate.

FOR QUESTIONS CALL 813-388-8735

PRINCIPAL DISPLAY PANEL - 15 Patch Carton

NDC 69833-011-15

Solmara
Lidocaine 4%,Menthol 5%

15
Patches